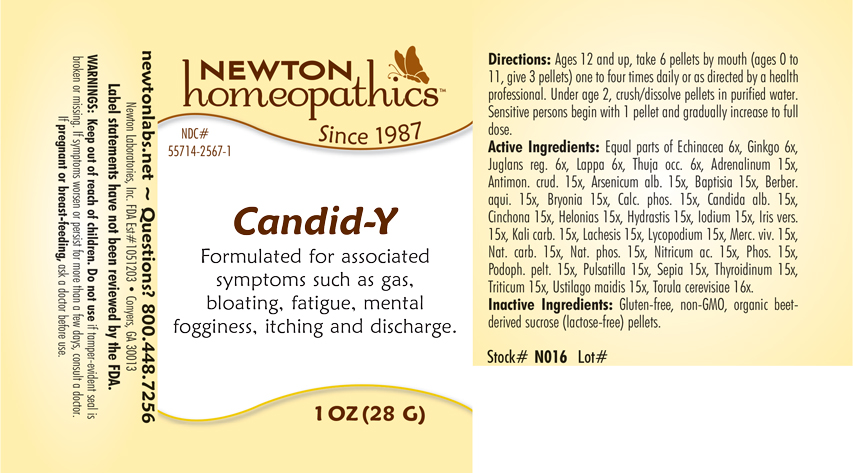 DRUG LABEL: Candid-Y
NDC: 55714-2567 | Form: PELLET
Manufacturer: Newton Laboratories, Inc.
Category: homeopathic | Type: HUMAN OTC DRUG LABEL
Date: 20210201

ACTIVE INGREDIENTS: EPINEPHRINE 15 [hp_X]/1 g; CANDIDA ALBICANS 15 [hp_X]/1 g; THYROID, UNSPECIFIED 15 [hp_X]/1 g; SACCHAROMYCES CEREVISIAE 16 [hp_X]/1 g; ELYMUS REPENS ROOT 15 [hp_X]/1 g; USTILAGO MAYDIS 15 [hp_X]/1 g; ANTIMONY TRISULFIDE 15 [hp_X]/1 g; ARSENIC TRIOXIDE 15 [hp_X]/1 g; BAPTISIA TINCTORIA 15 [hp_X]/1 g; MAHONIA AQUIFOLIUM ROOT BARK 15 [hp_X]/1 g; BRYONIA ALBA ROOT 15 [hp_X]/1 g; TRIBASIC CALCIUM PHOSPHATE 15 [hp_X]/1 g; CINCHONA OFFICINALIS BARK 15 [hp_X]/1 g; CHAMAELIRIUM LUTEUM ROOT 15 [hp_X]/1 g; GOLDENSEAL 15 [hp_X]/1 g; IODINE 15 [hp_X]/1 g; IRIS VERSICOLOR ROOT 15 [hp_X]/1 g; POTASSIUM CARBONATE 15 [hp_X]/1 g; LACHESIS MUTA VENOM 15 [hp_X]/1 g; LYCOPODIUM CLAVATUM SPORE 15 [hp_X]/1 g; MERCURY 15 [hp_X]/1 g; SODIUM CARBONATE 15 [hp_X]/1 g; SODIUM PHOSPHATE, DIBASIC, HEPTAHYDRATE 15 [hp_X]/1 g; NITRIC ACID 15 [hp_X]/1 g; PHOSPHORUS 15 [hp_X]/1 g; PODOPHYLLUM 15 [hp_X]/1 g; ANEMONE PULSATILLA 15 [hp_X]/1 g; SEPIA OFFICINALIS JUICE 15 [hp_X]/1 g; ECHINACEA, UNSPECIFIED 6 [hp_X]/1 g; GINKGO 6 [hp_X]/1 g; ENGLISH WALNUT 6 [hp_X]/1 g; ARCTIUM LAPPA ROOT 6 [hp_X]/1 g; THUJA OCCIDENTALIS LEAFY TWIG 6 [hp_X]/1 g
INACTIVE INGREDIENTS: SUCROSE

Candid-Y 2567P

WARNINGS SECTION

WARNINGS: Keep out of reach of children. Do not use if tamper-evident seal is broken or missing. If symptoms worsen or persist for more than a few days, consult a doctor. If pregnant or breast-feeding, ask a doctor before use.

OTC - KEEP OUT OF REACH OF CHILDREN SECTION

Keep out of reach of children.

OTC - PREGNANCY OR BREAST FEEDING SECTION

If pregnant or breast-feeding, ask a doctor before use.

QUESTIONS SECTION

newtonlabs.net - Questions? 800 448-7256

Newton Laboratories, Inc. FDA Est # 1051203 - Conyers, GA 30013

INACTIVE INGREDIENT SECTION

Glutun-free, non-GMO, organic beet-derived sucrose (lactose-free) pellets.

OTC - PURPOSE SECTION

Formulated for associated symptoms such as gas, bloating, fatigue mental fogginess, itching, and discharge.

OTC - ACTIVE INGREDIENT SECTION

Equal parts of Echinacea 6x, Ginkgo 6x, Juglans reg. 6x, Lappa 6x, Thuja occ. 6x, Antimon. crud. 15x, Baptisia 15x, Berber. aqui. 15x, Bryonia 15x, Calc. phos. 15x, Cinchona 15x, Helonias 15x, Hydrastis 15x, Iodium 15x, Iris vers. 15x, Kali carb. 15x, Lachesis 15x, Lycopodium 15x, Merc. viv. 15x, Nat.carb. 15x, Nat. phos. 15x, Nitricum ac. 15x, Phos. 15x, Podoph. pelt. 15x, Pulsatilla 15x, Sepia 15x, Adrenalinum 15x, Arsenicum alb. 15x, Candida alb.15x, Thyroidinum 15x, Triticum 15x, Ustilago maidis 15x, Torula cerevisiae 16x.

DOSAGE & ADMINISTRATION SECTION

Ages 12 and up, take 6 pellets by mouth (0 to 11, take 3 pellets) one to four times daily or as directed by a health professional. Under age 2, crush/dissolve pellets in purified water. Sensitive persons begin with 1 pellet and gradually increase to full dose.

INDICATIONS & USAGE SECTION

Formulated to associated symptoms such as gas, bloating, fatigue, mental fogginess, itching and discharge.